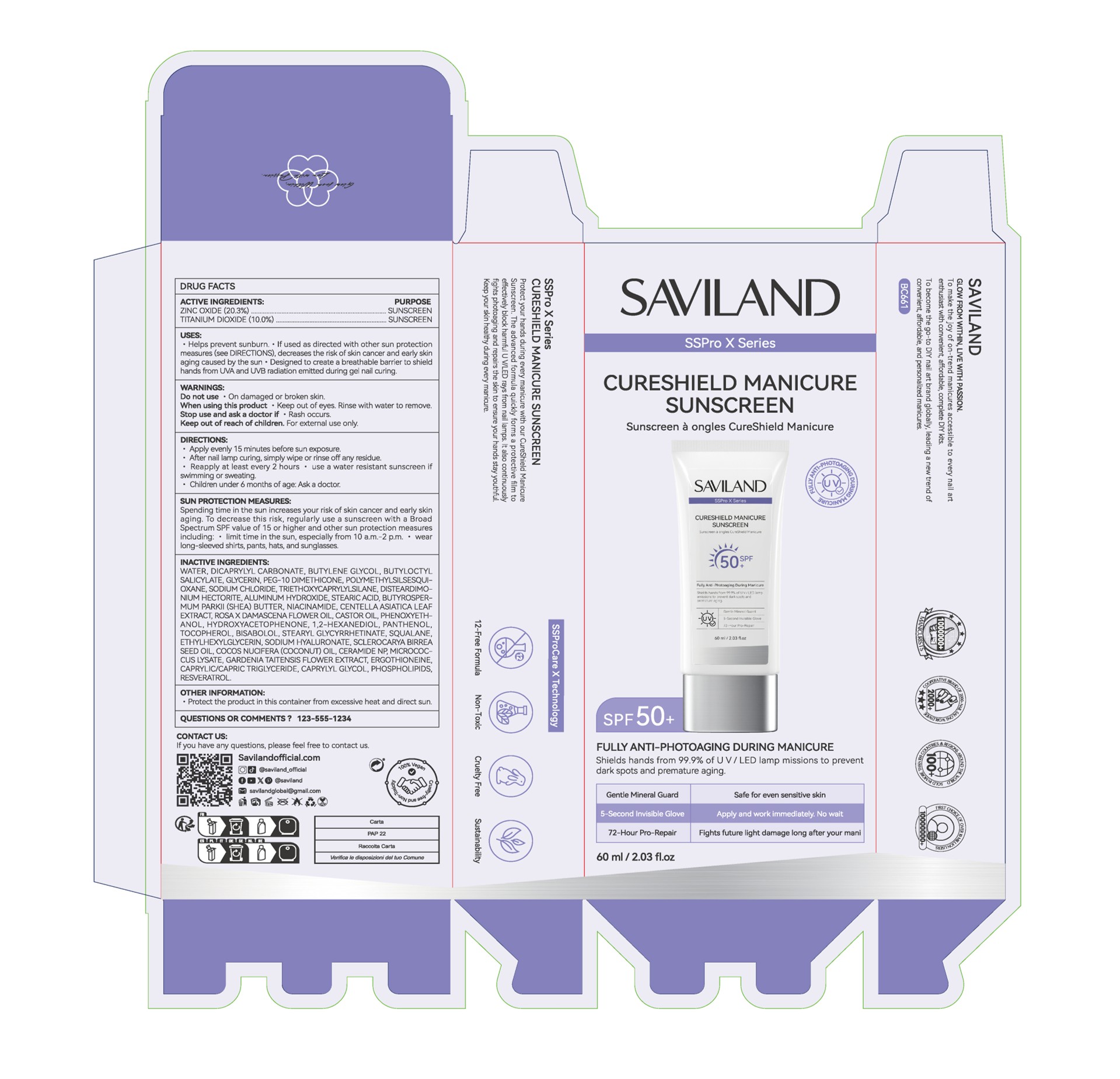 DRUG LABEL: CURESHIELD MANICURE SUNSCREEN
NDC: 85966-009 | Form: LOTION
Manufacturer: GUANGZHOU SAWEILAN IMPORT & EXPORT TRADING CO., LTD
Category: otc | Type: HUMAN OTC DRUG LABEL
Date: 20260118

ACTIVE INGREDIENTS: ZINC OXIDE 20.3 g/100 mL; TITANIUM DIOXIDE 10 g/100 mL
INACTIVE INGREDIENTS: STEARIC ACID; SODIUM CHLORIDE; CENTELLA ASIATICA; TOCOPHEROL; MICROCOCCUS LUTEUS; GARDENIA TAITENSIS FLOWER; SHEA BUTTER; CASTOR OIL; 1,2-HEXANEDIOL; PEG-10 DIMETHICONE (600 CST); HYDROXYACETOPHENONE; SODIUM HYALURONATE; ROSA X DAMASCENA FLOWER OIL; PHENOXYETHANOL; ETHYLHEXYLGLYCERIN; CAPRYLYL GLYCOL; BUTYLENE GLYCOL; NIACINAMIDE; WATER; PANTHENOL; CERAMIDE NP; STEARYL GLYCYRRHETINATE; DISTEARDIMONIUM HECTORITE; POLYMETHYLSILSESQUIOXANE (11 MICRONS); SCLEROCARYA BIRREA SEED OIL; COCOS NUCIFERA (COCONUT) OIL; EGG PHOSPHOLIPIDS; GLYCERIN; TRIETHOXYCAPRYLYLSILANE; ALUMINUM HYDROXIDE; SQUALANE; RESVERATROL; BISABOLOL; BUTYLOCTYL SALICYLATE; DICAPRYLYL CARBONATE; ERGOTHIONEINE; CAPRYLIC/CAPRIC TRIGLYCERIDE

85966-009 CURESHIELD MANICURE SUNSCREEN

ACTIVE INGREDIENT

ZINC OXIDE 20.3%
TITANIUM DIOXIDE 10%

PURPOSE

SUNSCREEN

INDICATIONS AND USAGE

Helps prevent sunburn, . lf used as directed with other sun protectionmeasures (see DIRECTlONS), decreases the risk of skin cancer and early skinaging caused by the sun *Designed to create a breathable barrier to shieldhands from UVA and UVB radiation emitted during gel nail curing.

WARNINGS

For external use only.

Do not use ·On damaged or broken skin.

When using this product · Keep out of eyes. Rinse with water to remove.

Stop use and ask a doctor if ·Rash occurs.

Keep out of reach of children.

DOSAGE AND ADMINISTRATION

Apply evenly 15 minutes before sun exposure.

After nail lamp curing, simply wipe or rinse off any residue.

Reapply at least every 2 hours *use a water resistant sunscreen if swimming or sweating.
Children under 6 months of age: Ask a doctor

INACTIVE INGREDIENT

WATER
DICAPRYLYL CARBONATE
BUTYLENE GLYCOL
BUTYLOCTYL SALICYLATE
GLYCERIN
PEG-10 DIMETHICONE
POLYMETHYLSILSESQUIOXANE
SODIUM CHLORIDE
TRIETHOXYCAPRYLYLSILANE
DISTEARDIMONIUM HECTORITE
ALUMINUM HYDROXIDE
STEARIC ACID
BUTYROSPERMUM PARKII (SHEA) BUTTER
NIACINAMIDE
CENTELLA ASIATICA LEAF EXTRACT
ROSA X DAMASCENA FLOWER OIL
CASTOR OIL
PHENOXYETHANOL
HYDROXYACETOPHENONE
1,2-HEXANEDIOL
PANTHENOL
TOCOPHEROL
BISABOLOL
STEARYL GLYCYRRHETINATE
SQUALANE
ETHYLHEXYLGLYCERIN
SODIUM HYALURONATE
SCLEROCARYA BIRREA SEED OIL
COCOS NUCIFERA (COCONUT) OIL
CERAMIDE NP
MICROCOCCUS LYSATE
GARDENIA TAITENSIS FLOWER EXTRACT
ERGOTHIONEINE
CAPRYLIC/CAPRIC TRIGLYCERIDE
CAPRYLYL GLYCOL
PHOSPHOLIPIDS
RESVERATROL